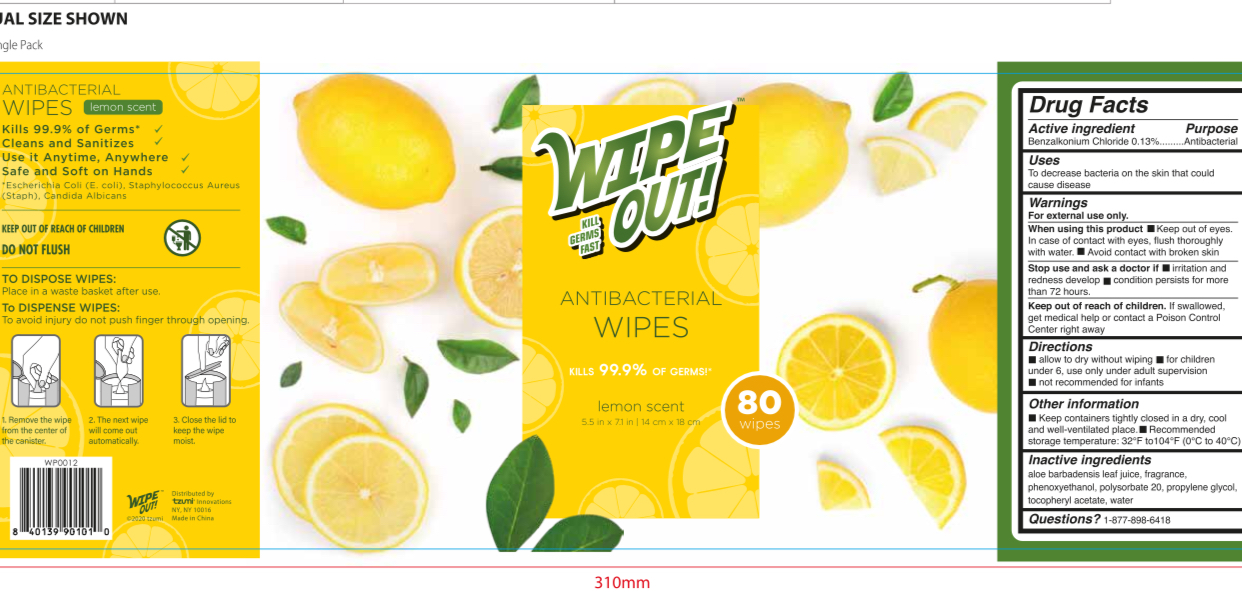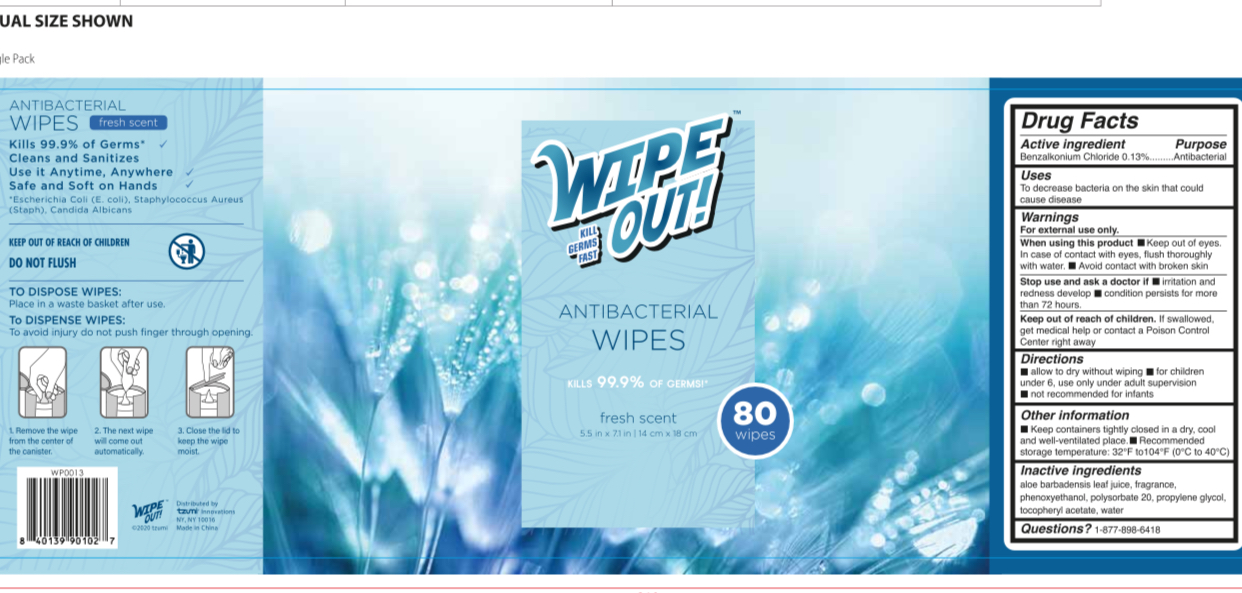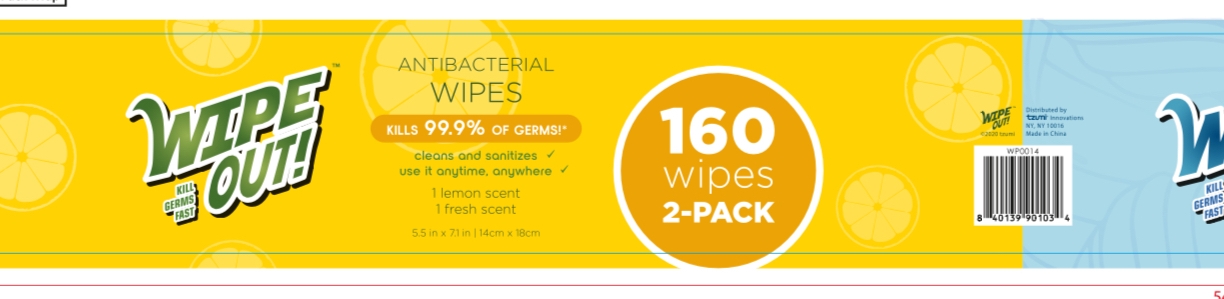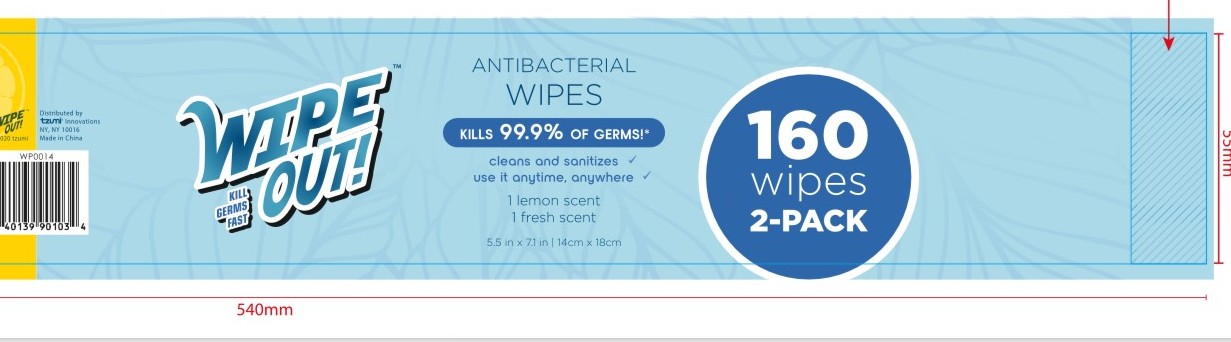 DRUG LABEL: WIPE OUT ANTIBACTERIAL WIPES 2 PACK 1 lemon scent 1 fresh scent
NDC: 77878-036 | Form: KIT | Route: TOPICAL
Manufacturer: TZUMI INNOVATIONS LLC
Category: otc | Type: HUMAN OTC DRUG LABEL
Date: 20201229

ACTIVE INGREDIENTS: BENZALKONIUM CHLORIDE 5.85 mg/1 1; BENZALKONIUM CHLORIDE 5.85 mg/1 1
INACTIVE INGREDIENTS: WATER; PROPYLENE GLYCOL; ALOE VERA LEAF; PHENOXYETHANOL; POLYSORBATE 20; .ALPHA.-TOCOPHEROL ACETATE; WATER; ALOE VERA LEAF; PROPYLENE GLYCOL; POLYSORBATE 20; PHENOXYETHANOL; .ALPHA.-TOCOPHEROL ACETATE

77878-034, 035, 036, Style WP0014 Kit

WIPE OUT ANTIBACTERIAL WIPES lemon scent

Active Ingredient

Benzalkonium Chloride 0.13%

Purpose

Antibacterial

Use

■ To decrease bacteria on the skin that could cause disease

WARNINGS

For external use only

When using this product, keep out of eyes
In case of contact with eyes, flush thoroughly with water

Avoid contact with broken skin

Stop Use

Stop use and ask a doctor if irritation and redness develop, condition persists for more than 72 hours

Keep out of reach of children. If swallowed, get medical help or contact a Poison Control Center right away

Directions

Wet hands thoroughly with product and allow to dry without wiping

For children under 6, use only under adult supervision

Not recommended for infants

Other information

Keep containers tightly closed in a dry, cool and well ventilated place
Recommended storage temperature: 32F to 104F (0C to 40C)

Inactive ingredients

Aloe Barbadensis Leaf Juice, Fragrance, Phenoxyethanol, Polysorbate 20, Propylene Glycol, Tocopheryl Acetate, Water

WIPE OUT ANTIBACTERIAL WIPES fresh scent

Active Ingredient

Benzalkonium Chloride 0.13%

Purpose

Antibacterial

Uses

To decreases bacteria on the skin that could cause disease

Warnings

For external use only

When using this product keep out of eyes. In case of contact with eyes, flush thoroughly with water.

Avoid contact with broken skin

Stop Use

Stop use and ask a doctor if irritation and redness develop, condition persists for more than 72 hours

Keep out of reach of children. If swallowed, get medical help or contact a Poison Control Center immediately

Directions

Wet hands thoroughly with product and allow to dry without wiping

For children under 6, use only under adult supervision

Not recommended for infants

Other Information

Keep containers tightly closed in a dry, cool and well ventilated place
Recommended storage temperature: 32F to 104F (0C to 40C)

Inactive Ingredients

Aloe Barbadensis Leaf Juice, Fragrance, Phenoxyethanol, Polysorbate 20, Propylene Glycol, Tocopheryl Acetate, Water